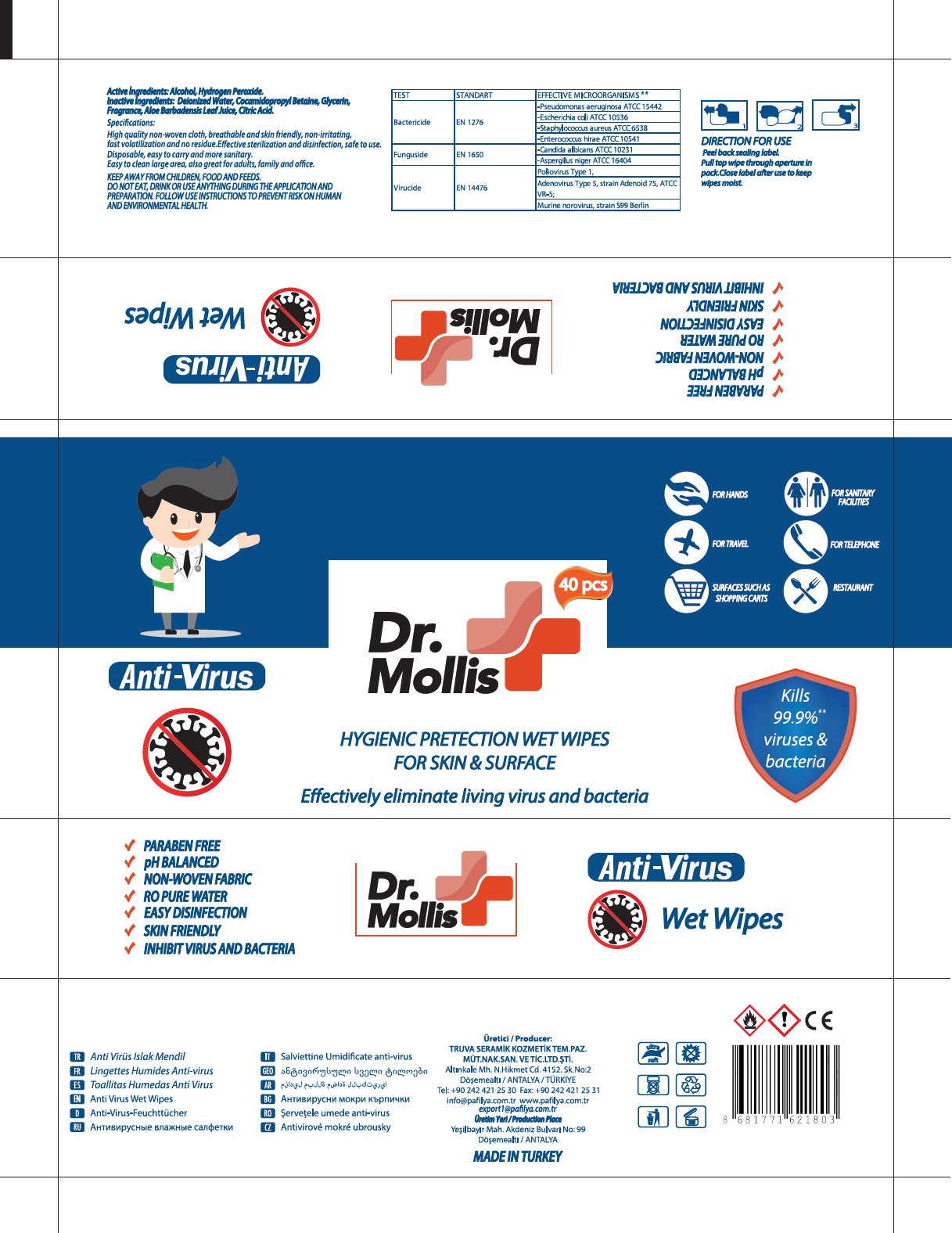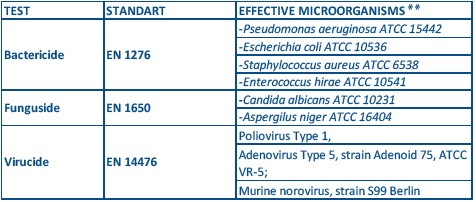 DRUG LABEL: Dr.Mollis
NDC: 79259-011 | Form: CLOTH
Manufacturer: TRUVA SERAMIK KOZMETIK TEMIZLIK PAZARLAMA MUTEAHHITLIK NAKLIYAT SANAYI VE TICARET LTD STI
Category: otc | Type: HUMAN OTC DRUG LABEL
Date: 20200706

ACTIVE INGREDIENTS: ALCOHOL 80 mL/100 mL; HYDROGEN PEROXIDE 0.12 g/100 mL
INACTIVE INGREDIENTS: WATER; COCAMIDOPROPYL BETAINE; GLYCERIN; ALOE VERA LEAF; CITRIC ACID MONOHYDRATE

Dr. Mollis Anti-Virus HYGIENIC PROTECTION WET WIPES

Active Ingredients: Alcohol, Hydrogen Peroxide

Purpose: Anti-Virus

INDICATIONS AND USAGE

Use: Decreases Virus

WARNINGS

DO NOT EAT, DRINK OR USE ANYTHING DURING THE APPLICATION AND PREPARATION. FOLLOW USE INSTRUCTIONS TO PREVENT RISK ON HUMAN AND ENVIRONMENTAL HEALTH.

KEEP AWAY FROM CHILDREN, FOOD AND FEEDS.

DIRECTION FOR USE

Peel back sealing label.

Pull top wipe through aperture in pack.Close label after use to keep wipes moist.

INACTIVE INGREDIENT

Inactive Ingredients: Deionized Water, Cocamidopropyl Betaine, Glycerin, Fragrance, Aloe Barbadensis Leaf Juice, Citric Acid.

HYGIENIC ROTECTION WET WIIPES FOR SKIN & SURFACE

Effectively eliminate living virus and bacteria

Kills 99.9%** viruses & bacteria

FOR HANDS

FOR TRAVEL

SURFACES SUCH AS SHOPPING CARTS

FOR SANITARY FACILITIES

FOR TELEPHONE

RESTAURANT

- PARABEN FREE
- pH BALANCED
- NON-WOVEN FABRIC
- RO PURE WATER
- EASY DISINFECTION
- SKIN FRIENDLY
- INHIBIT VIRUS AND BACTERIA

Specifications:

High quality non-woven cloth, breathable and skin friendly, non-irritating, fast volatilization and no residue.Effective sterilization and disinfection, safe to use.

Disposable, easy to carry and more sanitary.

Easy to clean large area, also great for adults, family and office.

Üretici / Producer:

TRUVA SERAMIK KOZMETIK TEM. PAZ.

MÜT.NAK.SAN.TIC.LTD.ŞTI.

Altınkale Mh. N. Hikmet Cd. 4152. Sk. No:2

Döşemealti / ANTALYA / TÜRKİYE

Tel: +90 242 421 25 30 Fax: +90 242 421 25 31

info@pafilya.com.tr www.pafilya.com.tr

export1@pafilya.com.tr

Üretim Yeri/Producer Place

yeşilbayir Mah. Akdeniz Bulvari No: 99

Döşemealti / ANTALYA

MADE IN TURKEY